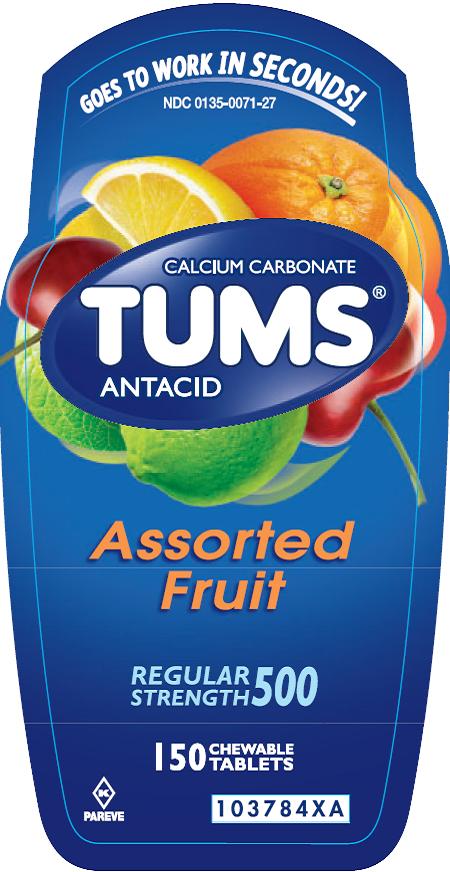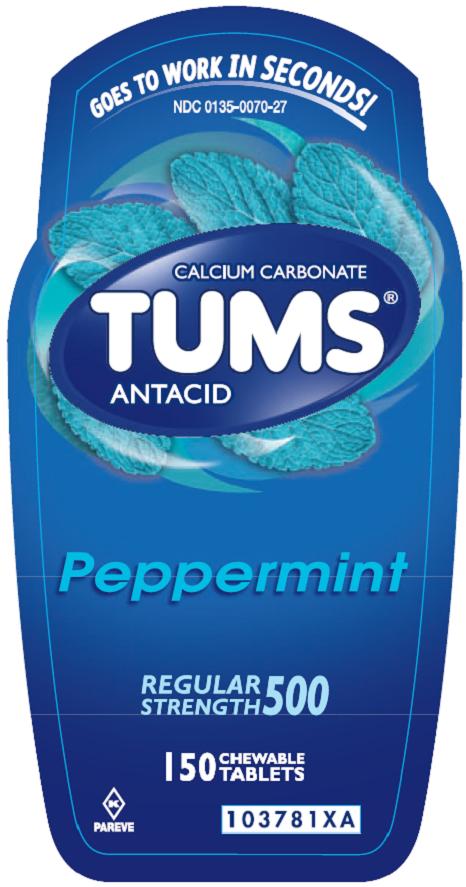 DRUG LABEL: TUMS
NDC: 0135-0071 | Form: TABLET
Manufacturer: Haleon US Holdings LLC
Category: otc | Type: HUMAN OTC DRUG LABEL
Date: 20240315

ACTIVE INGREDIENTS: CALCIUM CARBONATE 500 mg/1 1
INACTIVE INGREDIENTS: ADIPIC ACID; STARCH, CORN; FD&C BLUE NO. 1; FD&C RED NO. 40; FD&C YELLOW NO. 5; FD&C YELLOW NO. 6; MINERAL OIL; SODIUM POLYMETAPHOSPHATE; SUCROSE; TALC

Drug Facts

Active ingredient (per tablet)

Calcium Carbonate USP 500 mg

Purpose

Antacid

Uses

relieves

- heartburn
- acid indigestion
- sour stomach
- upset stomach associated with these symptoms

Warnings

Ask a doctor or pharmacist before use if you are

taking a prescription drug. Antacids may interact with certain prescription drugs.

When using this product

- do not take more than 15 tablets in 24 hours
- if pregnant do not take more than 10 tablets in 24 hours
- do not use the maximum dosage for more than 2 weeks except under the advice and supervision of a doctor

Directions

- adults and children 12 years of age and over: chew 2-4 tablets as symptoms occur, or as directed by a doctor
- do not take for symptoms that persist for more than 2 weeks unless advised by a doctor

Other information

- each tablet contains: elemental calcium 200mg
- store below 30oC (86oF)

Inactive ingredients (assorted fruit)

Adipic acid, corn starch, FD&C blue #1 lake, FD&C red #40 lake, FD&C yellow #5 (tartrazine) lake, FD&C yellow #6 lake, flavors, mineral oil, sodium polyphosphate, sucrose, talc

Inactive ingredient (peppermint)

corn starch, flavor, mineral oil, sodium polyphosphate, sucrose, talc

Questions?

1-800-897-7535

weekdays

Safety sealed- Do not use if printed inner seal beneath cap is missing or broken.

Gluten-Free

www.tums.com

GlaxoSmithKline

Moon Twp, PA 15108

PRINCIPAL DISPLAY PANEL

NDC 0135-0071-27

TUMS®

CALCIUM CARBONATE

ANTACID

REGULAR STRENGTH 500

Goes to Work in Seconds!

Assorted Fruit

150 CHEWABLE TABLETS

PAREVE

©2014 GSK

Front Label: 103784XA

Back Label: 103783XA

Principal Display Panel

NDC 0135-0070-27

TUMS®

CALCIUM CARBONATE

ANTACID

REGULAR STRENGTH 500

Goes to Work in Seconds!

Peppermint

150 CHEWABLE TABLETS

PAREVE

©2014 GSK

Front Label: 103781XA

Back Label: 103780XA